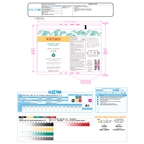 DRUG LABEL: NAS PORE REFINING SCRUB
NDC: 26052-040 | Form: EMULSION
Manufacturer: BURT'S BEES, INC.
Category: otc | Type: HUMAN OTC DRUG LABEL
Date: 20231005

ACTIVE INGREDIENTS: SALICYLIC ACID 1 g/100 g
INACTIVE INGREDIENTS: MEDIUM-CHAIN TRIGLYCERIDES; ALCOHOL; LECITHIN, SOYBEAN; PULLULAN; PHYTATE SODIUM; GLYCERIN; SALIX NIGRA BARK; COCONUT OIL; SHEA BUTTER; TOCOPHEROL; XANTHAN GUM; ANHYDROUS CITRIC ACID; WATER; PHENOXYETHANOL; STEARIC ACID; BETASIZOFIRAN; SUNFLOWER OIL; CARNAUBA WAX; SILICON DIOXIDE; SOYBEAN OIL; GLYCERYL STEARATE CITRATE; CENTELLA ASIATICA LEAF

NATURAL ACNE SOLUTIONS PORE REFINING SCRUB with Cica 285776.001

ACTIVE INGREDIENTS

SALICYLIC ACID 1.0%

PURPOSE

ACNE TREATMENT

Uses

• For the treatment of acne • Clears and helps
prevent acne blemishes, pimples, blackheads and
whiteheads

WARNINGS

For external use only.
• Skin irritation and dryness is more likely to occur if you use another topical acne medication at the same time. If irritation occurs, only one medication should be used unless directed by a doctor.

KEEP OUT OF REACH OF CHILDREN

IF SWALLOWED, GET MEDICAL HELP OR CONTACT A POISON CONTROL CENTER RIGHT AWAY.

Keep out of reach of children

If swallowed, get medical help or contact a Poison Control Center right away.

Directions

• Cover entire area with a thin layer one to two times a day, massage gently and rinse thoroughly • Avoid the eye area, if contact occurs rinse thoroughly with water • Because excessive dryness may occur, start with one application daily, then increase to two if needed or as directed by a doctor • If bothersome dryness or peeling occurs, reduce application to once a day or every other day

INACTIVE INGREDIENTS

water, helianthus annuus (sunflower) seed oil, glycerin, caprylic/capric triglyceride, cocos nucifera (coconut) oil, glyceryl stearate citrate, stearic acid, salix nigra (willow) bark extract, copernicia cerifera (carnauba) wax, butyrospermum parkii (shea) butter, centella asiatica leaf extract, xanthan gum, lecithin, sclerotium gum, pullulan, silica, tocopherol, glycine soja (soybean) oil, citric acid,
alcohol, fragrance*, sodium phytate, phenoxyethanol

QUESTIONS?

800-849-7112 OR WWW.BURTSBEES.COM

PDP

NATURAL ACNE SOLUTIONS

DEEP CLEANSING

Scrub

salicyclic acid acne treatment

with soothing cica

99% NATURAL ORIGIN

Net Wt. 4 oz / 113 g